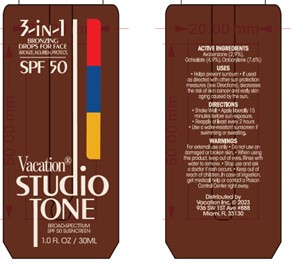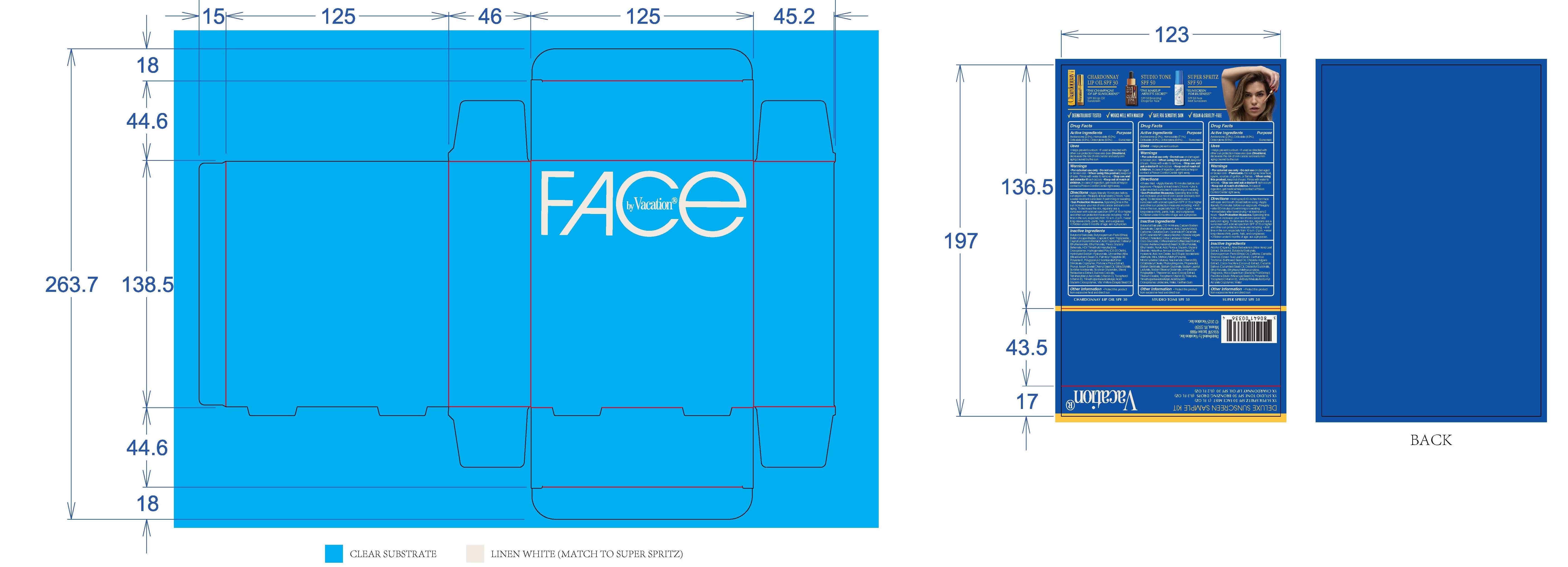 DRUG LABEL: Drops
NDC: 80641-013 | Form: LIQUID
Manufacturer: Vacation Inc.
Category: otc | Type: HUMAN OTC DRUG LABEL
Date: 20250220

ACTIVE INGREDIENTS: AVOBENZONE 2.9 g/100 mL; OCTISALATE 4.9 g/100 mL; OCTOCRYLENE 7.6 g/100 mL
INACTIVE INGREDIENTS: BUTYLOCTYL SALICYLATE

Vacation Studio Tone Bronzing Drops

Dosage and administration

Shake well

Apply liberally 15 minutes before sun exposure

Reapply at least every 2 hours

Use a water resistant sunscreen if swimming or sweating

Warning

For external use only

Do not use on damaged or broken skin

When using this product, keep out of eyes. Rinsed with water to remove.

Stop use and ask a doctor is rash occurs

Inactives

Butyloctyl Salicylate, C13-14 Alkane, Calcium Sodium Borosilicate, Caprylhydroxamic Acid, Caprylyl Glycol, Carbomer, Cellulose Gum, Ceramide AP, Ceramide EOP, Ceramide NP, Cetearyl Alcohol, Chlorella Vulgaris Extract, Cholesterol, Coco-Glucoside, Coffea Arabica (Coffee) Seed Extract , Corylus Avellana (Hazel) Seed Oil, Ethyl Ferulate, Ferulic Acid, Fragrance, Glycerin, Glyceryl Stearate, Helianthus Annuus (Sunflower) Seed Oil, Hyaluronic Acid, Iron Oxides, Mica, Microcrystalline Cellulose, Niacinamide

Octyldodecyl Oleate, Phytosphingosine, Propanediol, Sodium Benzoate, Sodium Gluconate, Sodium Lauroyl Lactylate

Sodium Stearoyl Glutamate, sr-Hydrozoan Polypeptide-1, Theobroma Cacao (Cocoa) Extract, Titanium Dioxide, Tocopherol, Tridecane

Trimethylpentanediol/Adipic Acid/Glycerin Crosspolymer, Undecane, Water, Xanthan Gum

Indications and Usage

Helps prevent sunburn

If used as directed with other sun protection measures (see Directions), decreases the risk of skin cancer and early skin aging caused by the sun

Keep out of reach of children

Purpose

Sunscreen